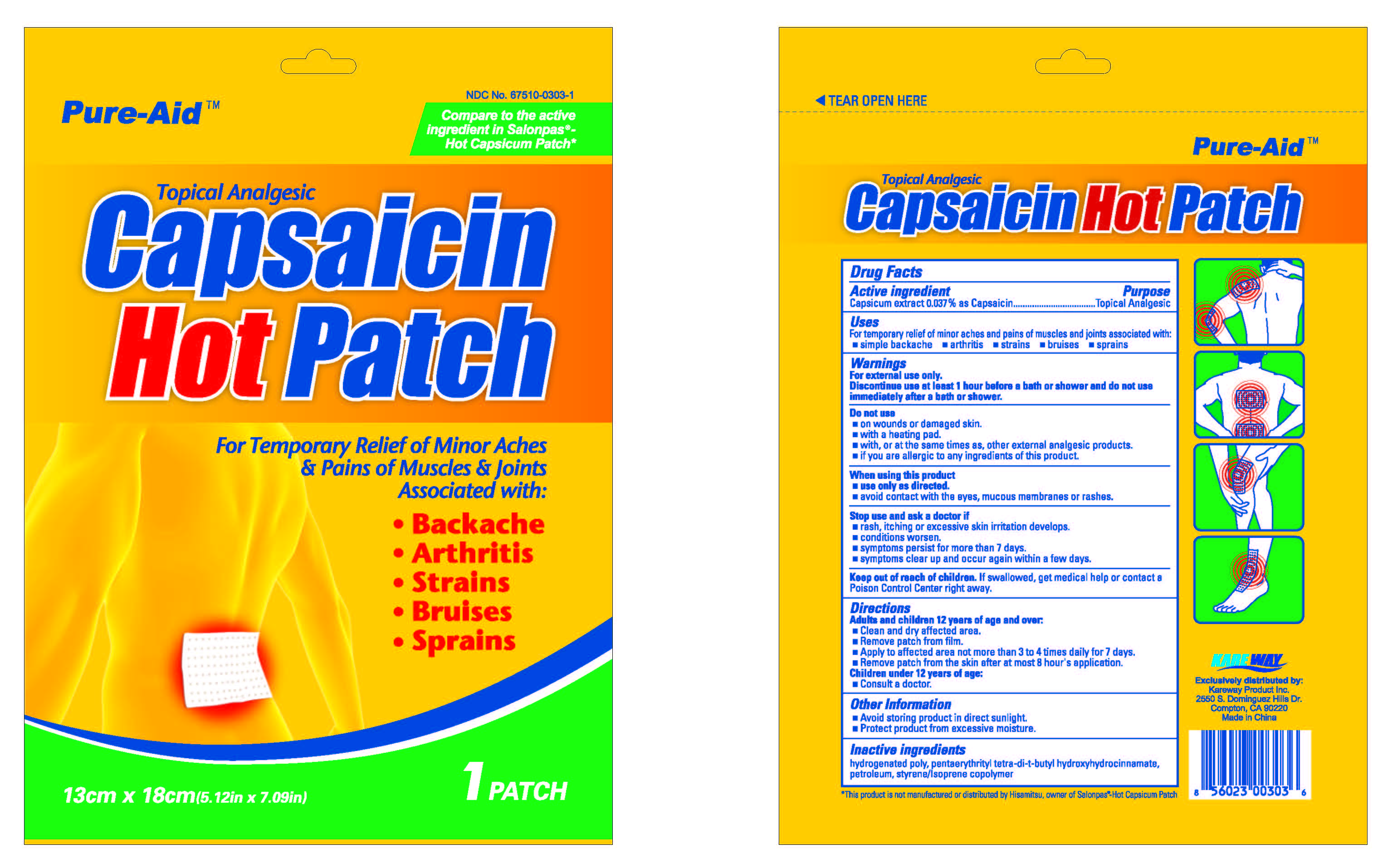 DRUG LABEL: Capsaicin Pain Relief
NDC: 67510-0303 | Form: PATCH
Manufacturer: Kareway Product, Inc.
Category: otc | Type: HUMAN OTC DRUG LABEL
Date: 20180607

ACTIVE INGREDIENTS: CAPSAICIN 0.702 mg/1 1
INACTIVE INGREDIENTS: HYDROGENATED POLYDECENE (550 MW); PENTAERYTHRITOL TETRAKIS(3-(3,5-DI-TERT-BUTYL-4-HYDROXYPHENYL)PROPIONATE); LIQUID PETROLEUM

Pure-Aid Capsaicin Pain Relief Patch

Active ingredient

Capsicum extract 0.025% as Capsaicin

Purpose

Topical analgesic

Uses

For temporary relief of minor aches and pains of muscles and joints associated with:

- simple backache
- arthritis
- strains
- bruises
- sprains

Warnings

For external use only.

Discontinue use at least 1 hour before a bath or shower and do not use immediately after a bath or shower.

Do not use

- on wounds or damaged skin
- with a heating pad
- with, or at the same times as other external analgesic products
- if you are allergic to any ingredients of this product

When using this product

- use only as directed
- avoid contact with the eyes, mucous membranes or rashes

Stop use and ask a doctor if

- rash, itching or excessive skin irritation develops
- conditions worsen
- symptoms persist for more than 7 days
- symptoms clear up and occur again within a few days

Keep out of reach of children.

If swallowed, get medical help or contact a Poison Control Center right away.

Directions

Adults and children 12 years of age and over:

- Clean and dry affected area
- Remove patch from film
- Apply to affected area not more than 3 to 4 times daily for 7 days
- Remove patch from the skin after at most 8 hour's application

Children under 12 years of age:

- Consult a doctor

Other information

- Avoid storing product in direct sunlight
- Protect product from excessive moisture

Inactive ingredients

hydrogenated poly, pentaerythrityl tetra-di-t-butyl hydroxyhydrocinnamate, petroleum, styrene/isoprene copolymer

Package label

Capsaicin Hot Patch